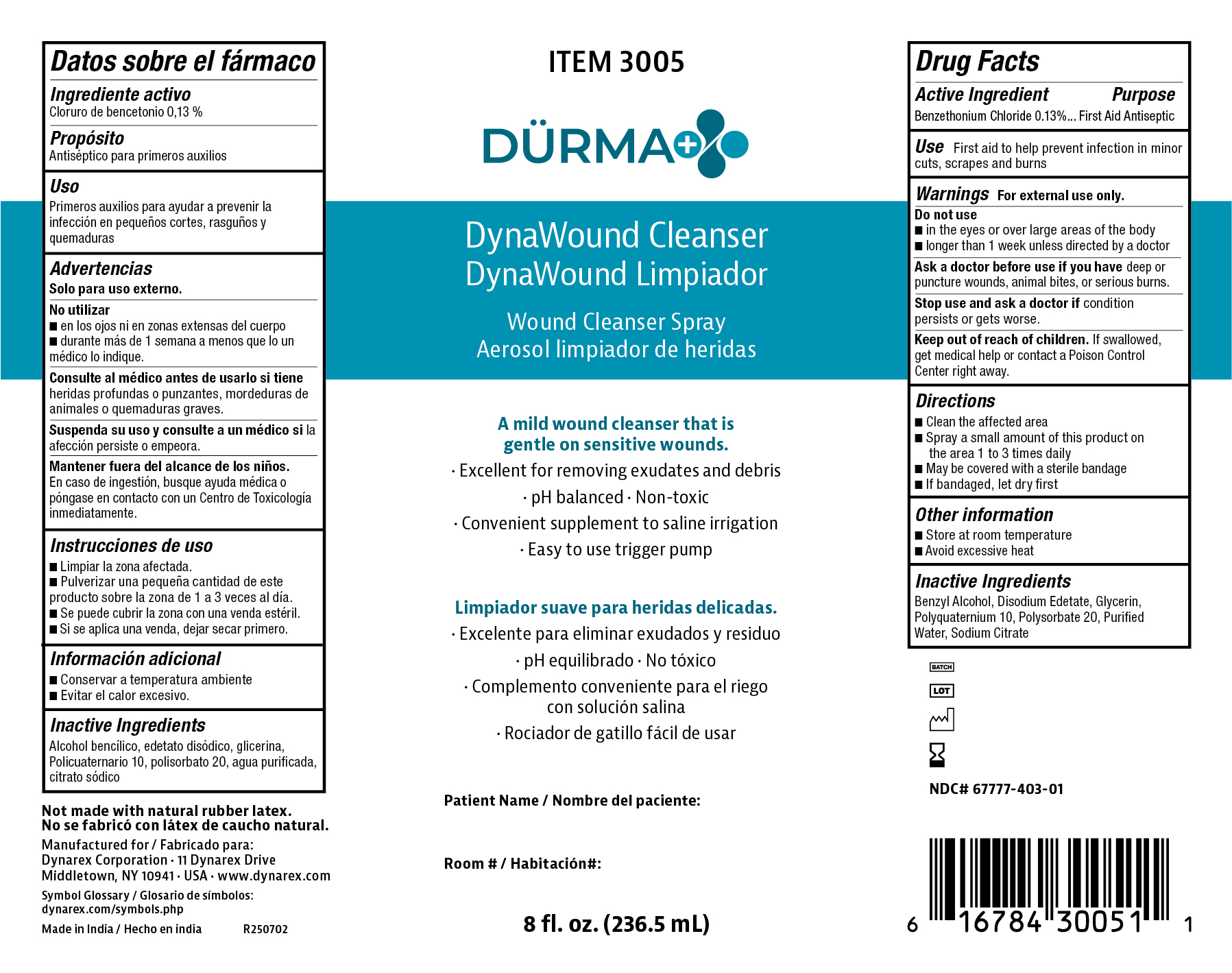 DRUG LABEL: DURMA DynaWound Cleanser
NDC: 67777-403 | Form: SPRAY
Manufacturer: Dynarex Corporation
Category: otc | Type: HUMAN OTC DRUG LABEL
Date: 20250708

ACTIVE INGREDIENTS: BENZETHONIUM CHLORIDE 0.13 g/100 mL
INACTIVE INGREDIENTS: BENZYL ALCOHOL; EDETATE DISODIUM; GLYCERIN; POLYQUATERNIUM-10 (125 MPA.S AT 2%); POLYSORBATE 20; SODIUM CITRATE; WATER

3005 Durma+ Brand - DynaWound Wound Cleanser Spray NDC 67777-403-01

Active Ingredient

Benzethonium Chloride 0.13%

Purpose

First Aid Antibiotic

Use(s)

First aid to help prevent infection in minor cuts, scrapes, and burns

Warnings

For External Use Only

Do not use

• In the eyes or over large areas of the body

• Longer than 1 week unless directed by a doctor

Ask a doctor before use if you have

deep or puncture wounds, animal bites, or serious burns.

Stop use and ask a doctor if

if condition persists or gets worse.

Keep out of reach of children

If swallowed, get medical help or contact a Poison Control Center (1-800-222-1222) right away.

Directions

• Clean the affected area

• Spray a small amount of this product on the area 1 to 3 times daily

• May be covered with a sterile bandage

• If bandaged let dry first

Other Information

• Store at room temperature 15°-30ºC (59º-86ºF)

• Avoid excessive heat

Inactive ingredients

Benzyl Alcohol, Disodium Edetate, Glycerin, Polyquaternium 10, Polysorbate 20, Purified Water, Sodium Citrate.

Label

Durma DynaWound Cleanser